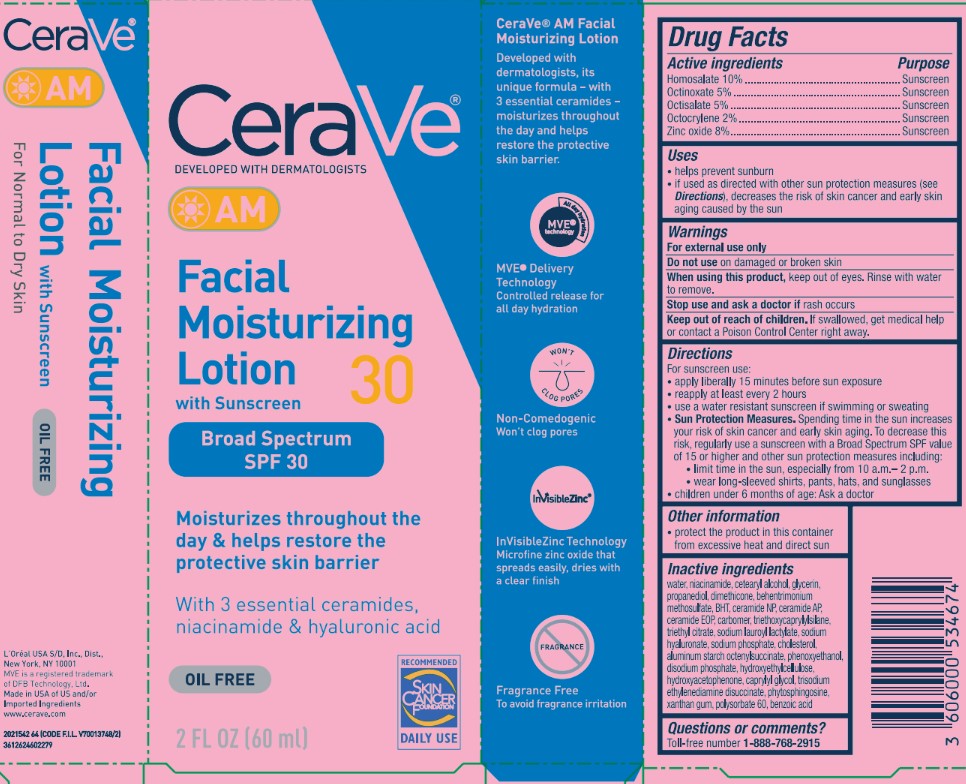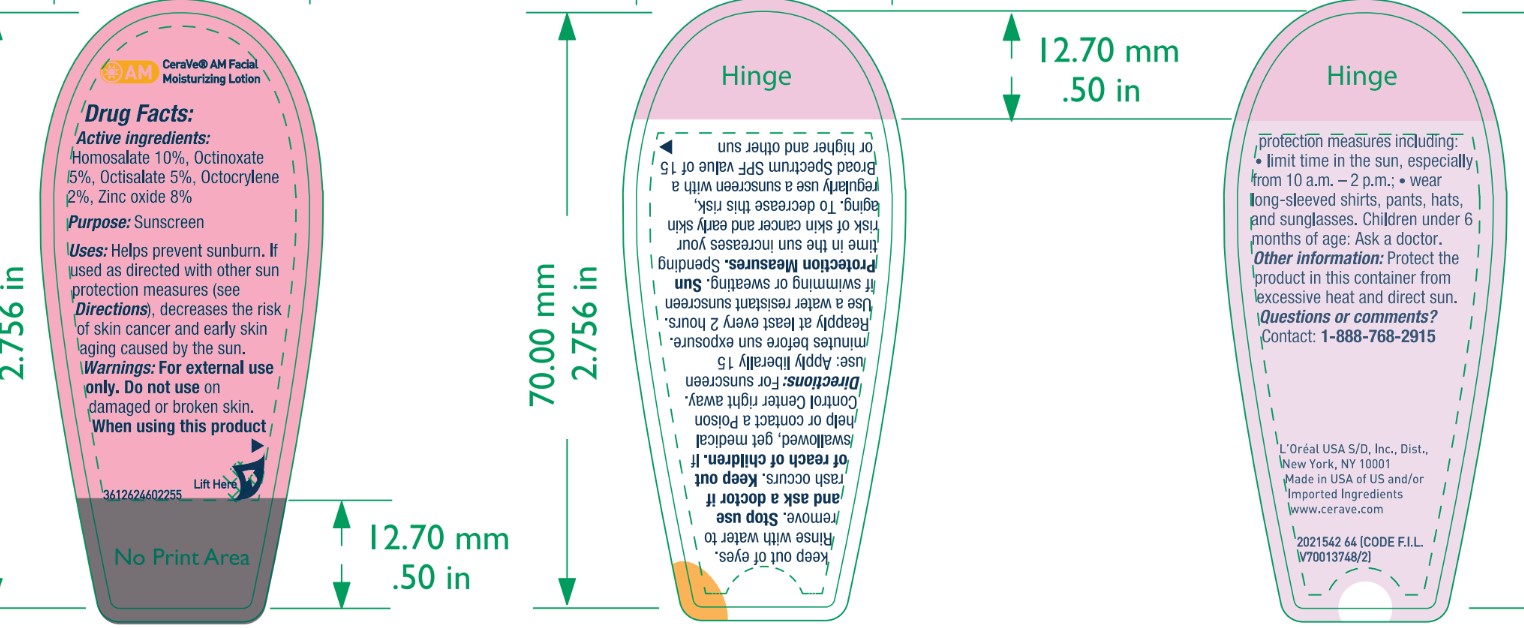 DRUG LABEL: CeraVe Facial Moisturizing with Sunscreen Broad Spectrum SPF 30
NDC: 49967-346 | Form: LOTION
Manufacturer: L’Oreal USA Products Inc
Category: otc | Type: HUMAN OTC DRUG LABEL
Date: 20250327

ACTIVE INGREDIENTS: HOMOSALATE 100 mg/1 mL; OCTINOXATE 50 mg/1 mL; OCTISALATE 50 mg/1 mL; OCTOCRYLENE 20 mg/1 mL; ZINC OXIDE 80 mg/1 mL
INACTIVE INGREDIENTS: WATER; NIACINAMIDE; CETEARYL ALCOHOL; GLYCERIN; PROPANEDIOL; DIMETHICONE; BEHENTRIMONIUM METHOSULFATE; BHT; CERAMIDE NP; CERAMIDE AP; CARBOMER; TRIETHOXYCAPRYLYLSILANE; TRIETHYL CITRATE; SODIUM LAUROYL LACTYLATE; SODIUM HYALURONATE; SODIUM PHOSPHATE; CHOLESTEROL; ALUMINUM STARCH OCTENYLSUCCINATE; PHENOXYETHANOL; DISODIUM PHOSPHATE; HYDROXYETHYLCELLULOSE; HYDROXYACETOPHENONE; CAPRYLYL GLYCOL; TRISODIUM ETHYLENEDIAMINE DISUCCINATE; PHYTOSPHINGOSINE; XANTHAN GUM; POLYSORBATE 60; BENZOIC ACID

Drug Facts

Active ingredients

Homosalate 10%
Octinoxate 5%
Octisalate 5%
Octocrylene 2%
Zinc oxide 8%

Purpose

Sunscreen

Uses

- helps prevent sunburn
- if used as directed with other sun protection measures (see Directions), decreases the risk of skin cancer and early skin aging caused by the sun

Warnings

For external use only

Do not use

on damaged or broken skin

When using this product,

keep out of eyes. Rinse with water to remove.

Stop use and ask a doctor if

rash occurs

Keep out of reach of children.

If swallowed, get medical help or contact a Poison Control Center right away.

Directions

For sunscreen use:

- apply liberally 15 minutes before sun exposure
- reapply at least every 2 hours
- use a water resistant sunscreen if swimming or sweating
- Sun Protection Measures. Spending time in the sun increases your risk of skin cancer and early skin aging. To decrease this risk, regularly use a sunscreen with a Broad Spectrum SPF value of 15 or higher and other sun protection measures including:
- limit time in the sun, especially from 10 a.m. - 2 p.m.
- wear long-sleeved shirts, pants, hats, and sunglasses
- children under 6 months of age: Ask a doctor

Other information

- protect the product in this container from excessive heat and direct sun

Inactive ingredients

water, niacinamide, cetearyl alcohol, glycerin, propanediol, dimethicone, behentrimonium methosulfate, BHT, ceramide NP, ceramide AP, ceramide EOP, carbomer, triethoxycaprylylsilane, triethyl citrate, sodium lauroyl lactylate, sodium hyaluronate, sodium phosphate, cholesterol, aluminum starch octenylsuccinate, phenoxyethanol, disodium phosphate, hydroxyethylcellulose, hydroxyacetophenone, caprylyl glycol, trisodium ethylenediamine disuccinate, phytosphingosine, xanthan gum, polysorbate 60, benzoic acid

Questions or comments?

Toll-free number 1-888-768-2915